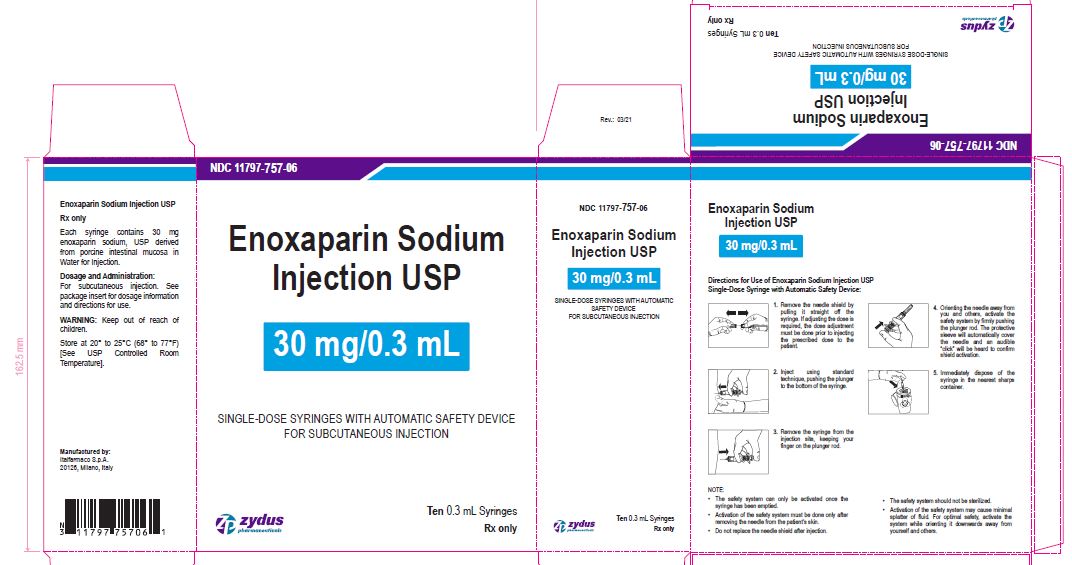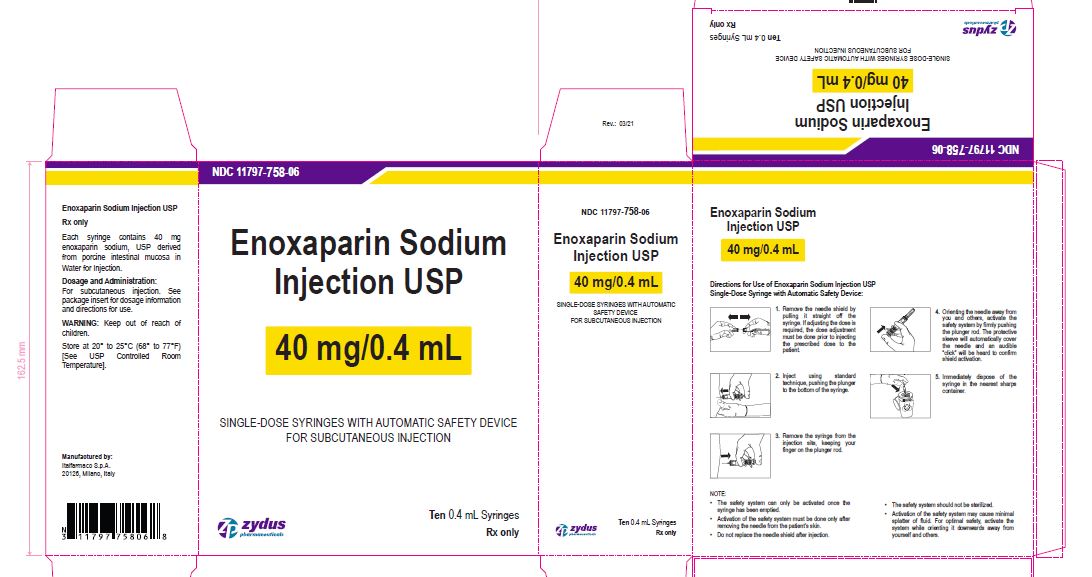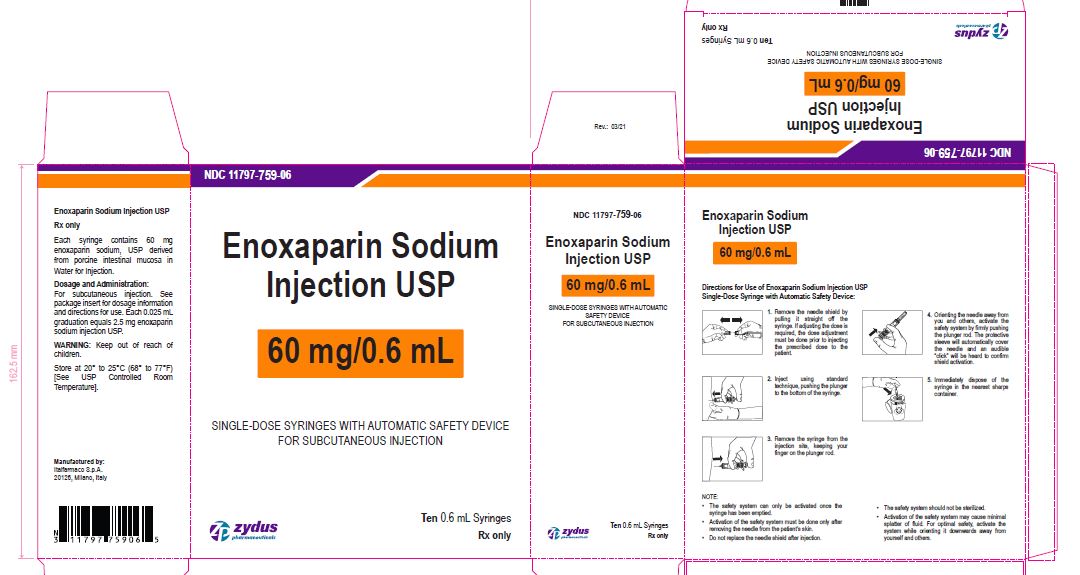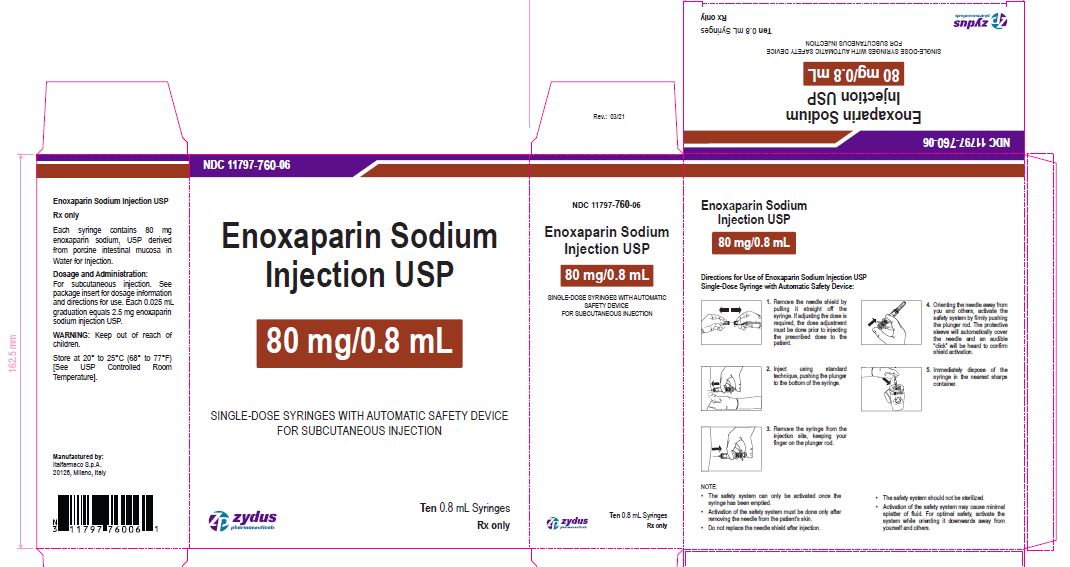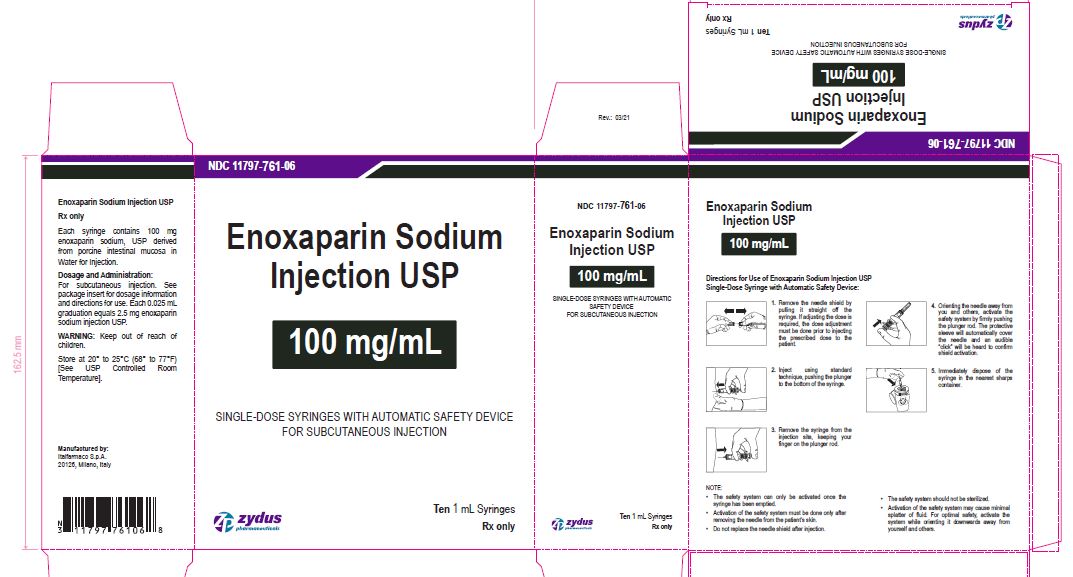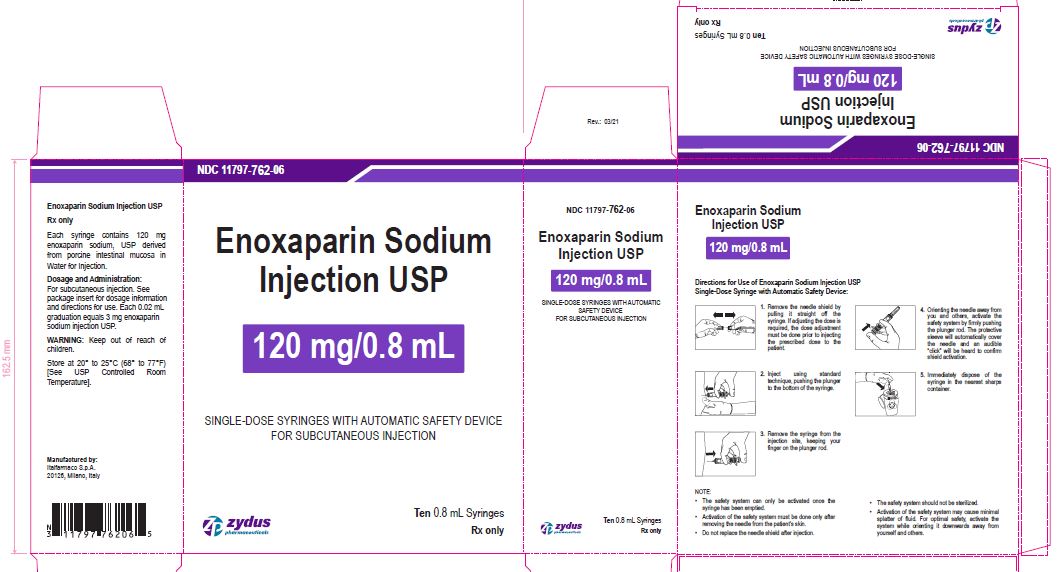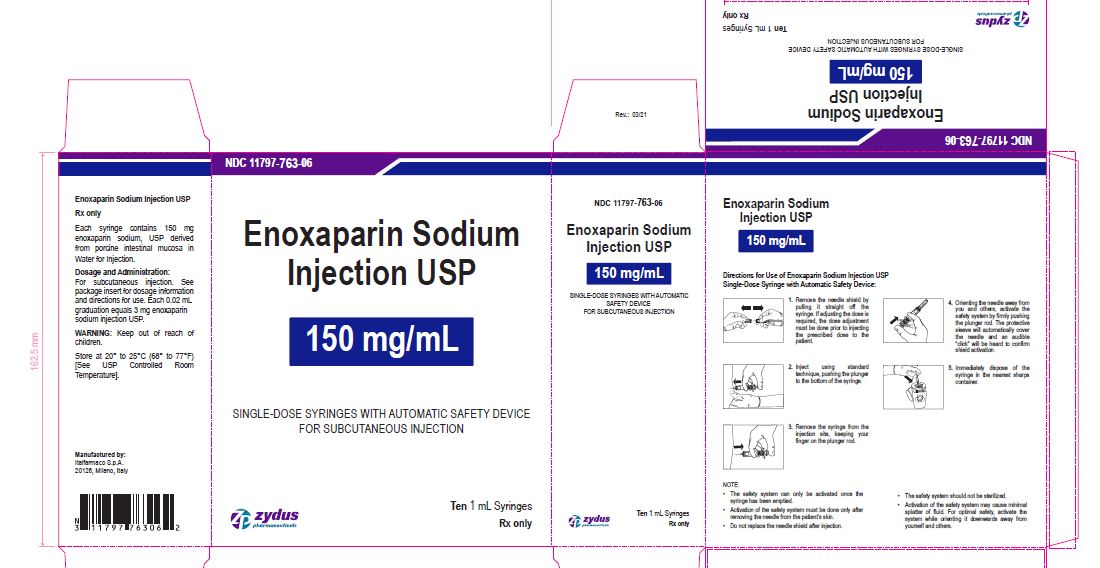 DRUG LABEL: Enoxaparin Sodium
NDC: 11797-757 | Form: INJECTION, SOLUTION
Manufacturer: Italfarmaco SpA
Category: prescription | Type: HUMAN PRESCRIPTION DRUG LABEL
Date: 20221105

ACTIVE INGREDIENTS: ENOXAPARIN SODIUM 30 mg/0.3 mL
INACTIVE INGREDIENTS: WATER

ENOXAPARIN SODIUM injection, for subcutaneous and intravenous use

PACKAGE LABEL.PRINCIPAL DISPLAY PANEL

NDC 11797-757-06

Enoxaparin Sodium Injection USP

30 mg/0.3 mL

SINGLE-DOSE SYRINGES WITH AUTOMATIC SAFETY DEVICE

FOR SUBCUTANEOUS INJECTION

Ten 0.3 mL Syringes

NDC 11797-758-06

Enoxaparin Sodium Injection USP

40 mg/0.4 mL

SINGLE-DOSE SYRINGES WITH AUTOMATIC SAFETY DEVICE

FOR SUBCUTANEOUS INJECTION

Ten 0.4 mL Syringes

NDC 11797-759-06

Enoxaparin Sodium Injection USP

60 mg/0.6 mL

SINGLE-DOSE SYRINGES WITH AUTOMATIC SAFETY DEVICE

FOR SUBCUTANEOUS INJECTION

Ten 0.6 mL Syringes

NDC 11797-760-06

Enoxaparin Sodium Injection USP

80 mg/0.8 mL

SINGLE-DOSE SYRINGES WITH AUTOMATIC SAFETY DEVICE

FOR SUBCUTANEOUS INJECTION

Ten 0.8 mL Syringes

NDC 11797-761-06

Enoxaparin Sodium Injection USP

100 mg/1 mL

SINGLE-DOSE SYRINGES WITH AUTOMATIC SAFETY DEVICE

FOR SUBCUTANEOUS INJECTION

Ten 1 mL Syringes

NDC 11797-762-06

Enoxaparin Sodium Injection USP

120 mg/0.8 mL

SINGLE-DOSE SYRINGES WITH AUTOMATIC SAFETY DEVICE

FOR SUBCUTANEOUS INJECTION

Ten 0.8 mL Syringes

NDC 11797-763-06

Enoxaparin Sodium Injection USP

150 mg/1 mL

SINGLE-DOSE SYRINGES WITH AUTOMATIC SAFETY DEVICE

FOR SUBCUTANEOUS INJECTION

Ten 1 mL Syringes